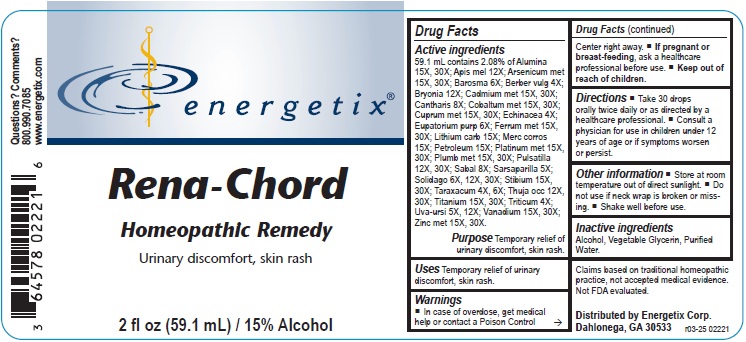 DRUG LABEL: Rena-Chord
NDC: 64578-0075 | Form: LIQUID
Manufacturer: Energetix Corporation
Category: homeopathic | Type: HUMAN OTC DRUG LABEL
Date: 20250715

ACTIVE INGREDIENTS: ALUMINUM OXIDE 15 [hp_X]/59.1 mL; APIS MELLIFERA 12 [hp_X]/59.1 mL; ARSENIC 15 [hp_X]/59.1 mL; AGATHOSMA BETULINA LEAF 6 [hp_X]/59.1 mL; BERBERIS VULGARIS ROOT BARK 4 [hp_X]/59.1 mL; BRYONIA ALBA ROOT 12 [hp_X]/59.1 mL; CADMIUM 15 [hp_X]/59.1 mL; LYTTA VESICATORIA 8 [hp_X]/59.1 mL; COBALT 15 [hp_X]/59.1 mL; COPPER 15 [hp_X]/59.1 mL; ECHINACEA ANGUSTIFOLIA 4 [hp_X]/59.1 mL; EUTROCHIUM PURPUREUM ROOT 6 [hp_X]/59.1 mL; IRON 15 [hp_X]/59.1 mL; LITHIUM CARBONATE 15 [hp_X]/59.1 mL; MERCURIC CHLORIDE 15 [hp_X]/59.1 mL; KEROSENE 15 [hp_X]/59.1 mL; PLATINUM 15 [hp_X]/59.1 mL; LEAD 15 [hp_X]/59.1 mL; PULSATILLA VULGARIS 12 [hp_X]/59.1 mL; SAW PALMETTO 8 [hp_X]/59.1 mL; SARSAPARILLA 5 [hp_X]/59.1 mL; SOLIDAGO VIRGAUREA FLOWERING TOP 6 [hp_X]/59.1 mL; ANTIMONY 15 [hp_X]/59.1 mL; TARAXACUM OFFICINALE 4 [hp_X]/59.1 mL; THUJA OCCIDENTALIS LEAFY TWIG 12 [hp_X]/59.1 mL; TITANIUM 15 [hp_X]/59.1 mL; ELYMUS REPENS ROOT 4 [hp_X]/59.1 mL; ARCTOSTAPHYLOS UVA-URSI LEAF 5 [hp_X]/59.1 mL; VANADIUM 15 [hp_X]/59.1 mL; ZINC 15 [hp_X]/59.1 mL
INACTIVE INGREDIENTS: WATER; GLYCERIN; ALCOHOL

Rena-Chord

ACTIVE INGREDIENT

Active ingredients59.1 mL contains 2.08% of: Alumina 15X, 30X; Apis mel 12X; Arsenicum met 15X, 30X; Barosma 6X; Berber vulg 4X; Bryonia 12X; Cadmium met 15X, 30X; Cantharis 8X; Cobaltum met 15X, 30X; Cuprum met 15X, 30X; Echinacea 4X; Eupatorium purp 6X; Ferrum met 15X, 30X; Lithium carb 15X; Merc corros 15X; Petroleum 15X; Platinum met 15X, 30X; Plumb met 15X, 30X; Pulsatilla 12X, 30X; Sabal 8X; Sarsaparilla 5X; Solidago 6X, 12X, 30X; Stibium 15X, 30X; Taraxacum 4X, 6X; Thuja occ 12X, 30X; Titanium 15X, 30X; Triticum 4X; Uva-ursi 5X, 12X; Vanadium 15X, 30X; Zinc met 15X, 30X.

Claims based on traditional homeopathic practice, not accepted medical evidence. Not FDA evaluated.

Uses

Temporary relief of urinary discomfort, skin rashes.

Warnings

- In case of overdose, get medical help or contact a Poison Control Center right away.
- If pregnant or breast-feeding, ask a health professional before use.

• Keep out of reach of children.

Directions

- Take 30 drops orally twice daily or as directed by a healthcare professional.
- Consult a physician for use in children under 12 years of age or if symptoms worsen or persist.

Other information

- Store at room temperature out of direct sunlight.
- Do not use if neck wrap is broken or missing.
- Shake well before use.

Inactive ingredients

Alcohol, Vegetable Glycerin, Purified Water.

QUESTIONS

Distributed by Energetix Corp.

Dahlonega, GA 30533

Questions? Comments?

800.990.7085

www.energetix.com

PACKAGE LABEL

energetix

Rena-Chord

Homeopathic Remedy

Urinary discomfort, skin rash

2 fl oz (59.1 mL) / 15% Alcohol

Purpose Temporary relief of urinary discomfort, skin rash.